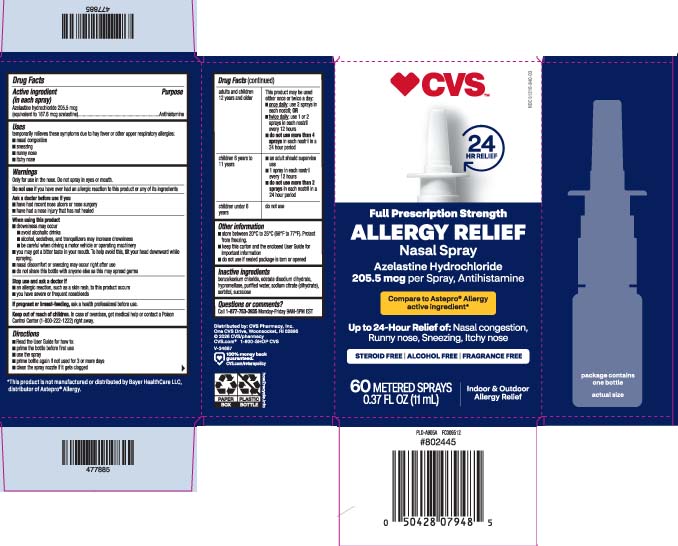 DRUG LABEL: Azelastine Hydrochloride
NDC: 51316-840 | Form: SPRAY, METERED
Manufacturer: CVS PHARMACY, INC
Category: otc | Type: HUMAN OTC DRUG LABEL
Date: 20260106

ACTIVE INGREDIENTS: AZELASTINE HYDROCHLORIDE 205.5 ug/1 1
INACTIVE INGREDIENTS: BENZALKONIUM CHLORIDE; EDETATE DISODIUM; HYPROMELLOSE, UNSPECIFIED; SODIUM CITRATE, UNSPECIFIED FORM; WATER; SORBITOL; SUCRALOSE

Drug Facts

Active ingredient (in each spray)

Azelastine hydrochloride 205.5 mcg (equivalent to 187.6 mcg azelastine)

Purpose

Antihistamine

Uses

temporarily relieves these symptoms due to hay fever or other upper respiratory allergies:

- nasal congestion
- sneezing
- runny nose
- itchy nose

Warnings

Only for use in the nose. Do not spray in eyes or mouth.

Do not use

if you have ever had an allergic reaction to this product or any of its ingredients

Ask a doctor before use if you

- have had recent nose ulcers or nose surgery
- have had nose injury that has not healed

When using this product

- drowsiness may occur
  - avoid alcoholic drinks
  - alcohol, sedatives, and tranquilizers may increase drowsiness
  - be careful when driving a motor vehicle or operating machinery
- you may get a bitter taste in your mouth. To help avoid this, tilt your head downward while spraying.
- nasal discomfort or sneezing may occur right after use
- do not share this bottle with anyone else as this may spread germs

Stop use and ask a doctor if

- an allergic reaction, such as a skin rash, to this product occurs
- you have severe or frequent nosebleeds

If pregnant or breast-feeding,

ask a health professional before use.

Keep out of reach of children.

In case of overdose, get medical help or contact a Poison Control Center (1-800-222-1222) right away.

Directions

- Read the User Guide for how to:
  - prime the bottle before first use
  - use the spray
  - prime bottle again if not used for 3 or more days
  - clean the spray nozzle if it gets clogged

adults and children 12 years and older | This product may be used either once or twice a day:; - once daily: use 2 sprays in each nostril; OR - twice daily: use 1 or 2 sprays in each nostril every 12 hours - do not use more than 4 sprays in each nostril in a 24 hour period
children 6 years to 11 years | - an adult should supervise use - 1 spray in each nostril every 12 hours - do not use more than 2 sprays in each nostril in a 24 hour period
children under 6 years | do not use

Other information

- store between 20°C to 25°C (68°F to 77°F). Protect from freezing.
- keep this carton and the enclosed User Guide for important information
- do not use if sealed package is torn or opened

Inactive ingredients

benzalkonium chloride, edetate disodium dihydrate, hypromellose, purified water, sodium citrate (dihydrate), sorbitol, sucralose

Questions or comments?

call 1-877-753-3935 Monday-Friday 9AM-5PM EST

Principal display panel

*Compare to Astepro® Allergy active ingredient*

Full prescription Strength

ALLERGY RELIEF

Nasal Spray

Azelastine Hydrochloride

205.5 mcg per spray, Antihistamine

Up to 24-hour relief of

Nasal congestion

Runny nose

Sneezing

Itchy nose

STEROID FREE | ALCOHOL FREE | FRAGRANCE FREE

METERED SPRAYS

Indoor & Outdoor Allergy Relief

FL OZ (mL)

*This product is not manufactured or distributed by Bayer Healthcare LLC, distributor of Astepro® Allergy Spray.

Distributed by: CVS Pharmacy, Inc.

One CVS Drive, Woonsocket, RI 02895

Package label

CVS Allergy Relief Nasal Spray